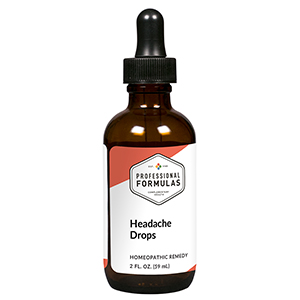 DRUG LABEL: Headache Drops
NDC: 63083-2027 | Form: LIQUID
Manufacturer: Professional Complementary Health Formulas
Category: homeopathic | Type: HUMAN OTC DRUG LABEL
Date: 20190815

ACTIVE INGREDIENTS: ONION 3 [hp_X]/59 mL; GELSEMIUM SEMPERVIRENS ROOT 3 [hp_X]/59 mL; AMARYLLIS BELLADONNA WHOLE 4 [hp_X]/59 mL; STRYCHNOS NUX-VOMICA SEED 4 [hp_X]/59 mL; SPIGELIA ANTHELMIA WHOLE 4 [hp_X]/59 mL; COFFEA ARABICA SEED, ROASTED 6 [hp_X]/59 mL; LYCOPODIUM CLAVATUM SPORE 6 [hp_X]/59 mL; LACHESIS MUTA VENOM 8 [hp_X]/59 mL; PULSATILLA MONTANA WHOLE 8 [hp_X]/59 mL; NITROGLYCERIN 12 [hp_X]/59 mL; SODIUM CHLORIDE 12 [hp_X]/59 mL
INACTIVE INGREDIENTS: ALCOHOL; WATER

C27

ACTIVE INGREDIENTS

Allium cepa 3X
Gelsemium sempervirens 3X
Belladonna 4X
Nux vomica 4X
Spigelia anthelmia 4X
Coffea tosta 6X
Lycopodium clavatum 6X
Lachesis mutus 8X
Pulsatilla 8X
Glonoinum 12X
Natrum muriaticum 12X

QUESTIONS

Professional Formulas

PO Box 2034 Lake Oswego, OR 97035

INDICATIONS

For the temporary relief of occasional headaches.*

PURPOSE

*Claims based on traditional homeopathic practice, not accepted medical evidence. Not FDA evaluated.

WARNINGS

Consult a doctor if condition worsens or if symptoms persist. Keep out of the reach of children. In case of overdose, get medical help or contact a poison control center right away. If pregnant or breastfeeding, ask a healthcare professional before use.

Keep out of the reach of children.

PREGNANCY OR BREAST FEEDING

If pregnant or breastfeeding, ask a healthcare professional before use.

DIRECTIONS

Place drops under tongue 30 minutes before/after meals. Adults and children 12 years and over: Take 10 drops up to 3 times per day for up to 6 weeks. For immediate onset of symptoms, take 10 to 15 drops every 15 minutes up to 3 hours. For less severe symptoms, take 10-15 drops hourly up to 8 hours. Consult a physician for use in children under 12 years of age.

OTHER INFORMATION

Tamper resistant. If seal is broken, do not use. After opening, close container tightly and store at room temperature away from heat.

INACTIVE INGREDIENTS

20% ethanol, purified water.

LABEL

Est 1985

Professional Formulas

Complementary Health

Headache Drops

Homeopathic Remedy

2 FL. OZ. (59 mL)